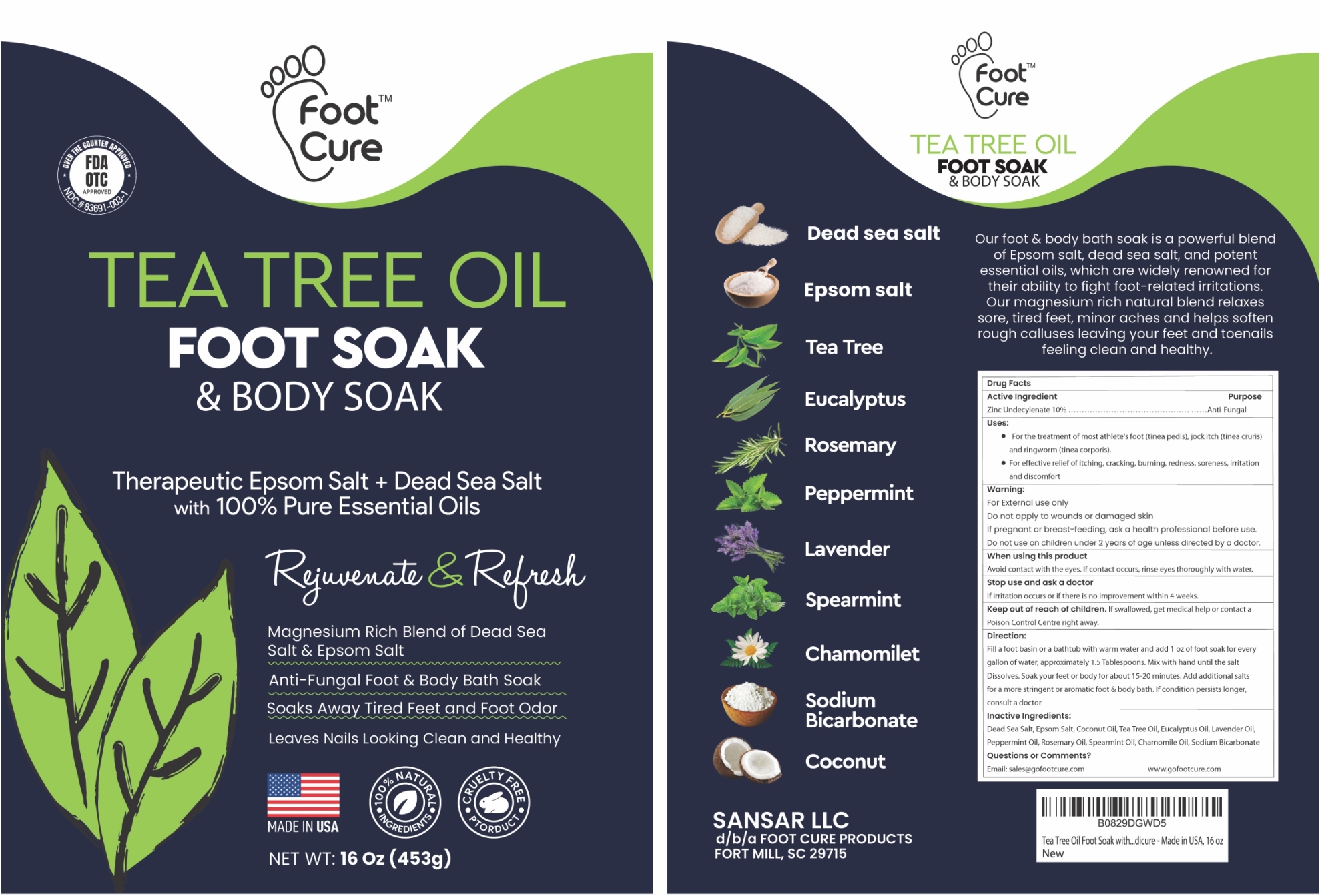 DRUG LABEL: Tea Tree Oil Foot Soak and Body Soak
NDC: 83691-003 | Form: GRANULE
Manufacturer: SANSAR, LLC
Category: otc | Type: HUMAN OTC DRUG LABEL
Date: 20250328

ACTIVE INGREDIENTS: Zinc Undecylenate 10 g/100 g
INACTIVE INGREDIENTS: SEA SALT; MAGNESIUM SULFATE HEPTAHYDRATE; COCONUT OIL; TEA TREE OIL; EUCALYPTUS OIL; Lavender Oil; PEPPERMINT OIL; ROSEMARY OIL; SPEARMINT OIL; CHAMOMILE FLOWER OIL; Sodium Bicarbonate

Tea Tree Oil Foot Soak and Body Soak

Active Ingredient

Zinc Undecylenate 10%

Purpose

Anti-Fungal

Uses

- For the treatment of most athlete's foot (tinea pedis), jock itch (tinea cruris) and ringworm (tinea corporis).
- For effective relief of itching, cracking, burning, redness, soreness, irritation and discomfort

Warning

For External use only
Do not apply to wounds or damaged skin
If pregnant or breast-feeding, ask a health professional before use.
Do not use on children under 2 years of age unless directed by a doctor.

When using this product Avoid contact with the eyes. If contact occurs, rinse eyes thoroughly with water.

Stop use and ask a doctor If irritation occurs or if there is no improvement within 4 weeks.

Keep out of reach of children. If swallowed, get medical help or contact a Poison Control Centre right away.

Direction

Fill a foot basin or a bathtub with warm water and add 1 oz of foot soak for every gallon of water, approximately 1.5 Tablespoons. Mix with hand until the salt Dissolves. Soak your feet or body for about 15-20 minutes. Add additional salts for a more stringent or aromatic foot & body bath. If condition persists longer, consult a doctor

Inactive Ingredients

Dead Sea Salt, Epsom Salt, Coconut Oil, Tea Tree Oil, Eucalyptus Oil, Lavender Oil, Peppermint Oil, Rosemary Oil, Spearmint Oil, Chamomile Oil, Sodium Bicarbonate

Questions or Comments?

Email: sales@gofootcure.com or www.gofootcure.com